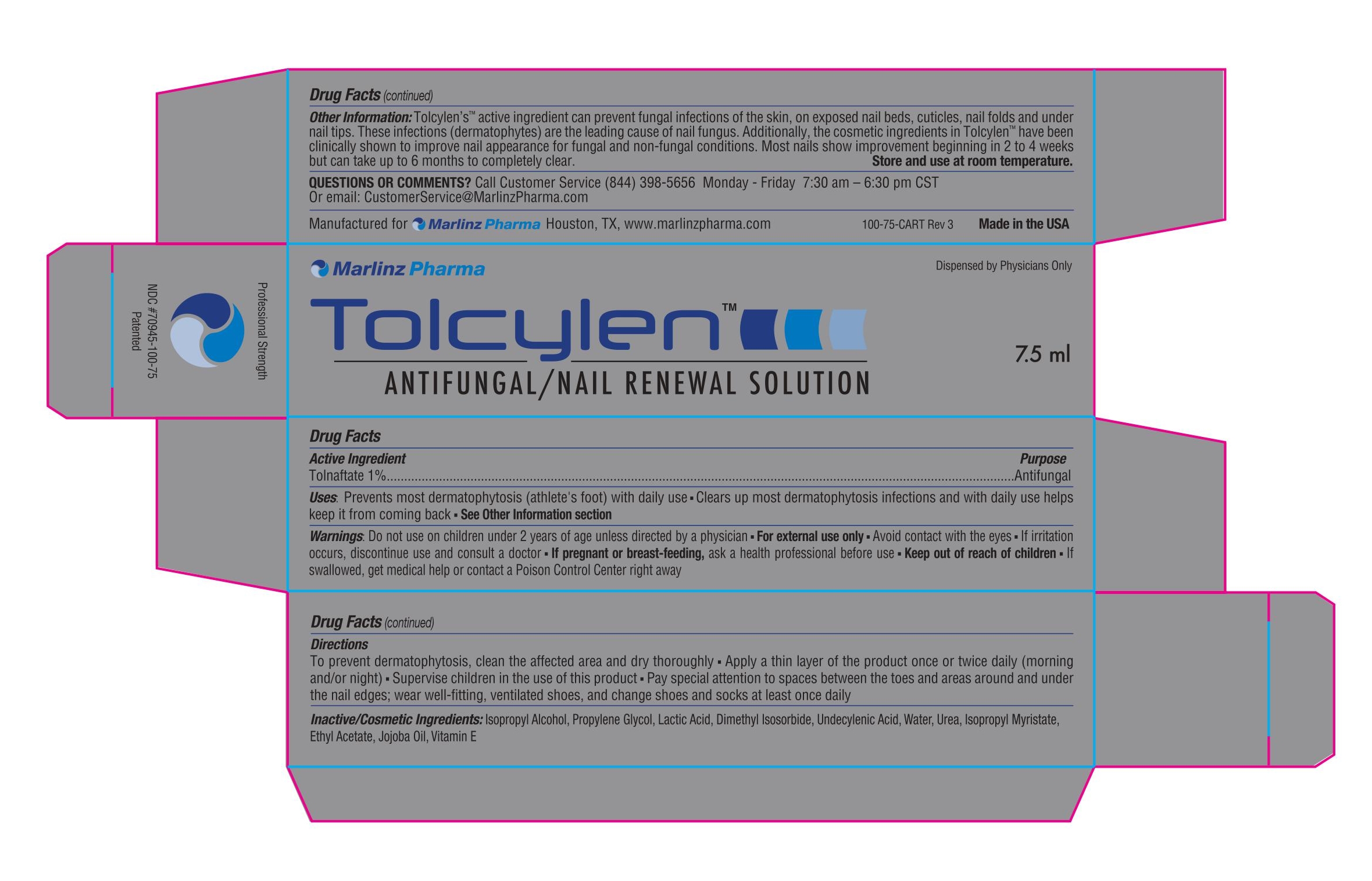 DRUG LABEL: Tolcylen Antifungal Solution
NDC: 70945-100 | Form: SOLUTION
Manufacturer: Marlinz Pharma, LLC
Category: otc | Type: HUMAN OTC DRUG LABEL
Date: 20220201

ACTIVE INGREDIENTS: TOLNAFTATE 1 mg/100 mL
INACTIVE INGREDIENTS: DIMETHYL ISOSORBIDE; ISOPROPYL ALCOHOL; ISOPROPYL MYRISTATE; LACTIC ACID; ETHYL ACETATE; UREA; UNDECYLENIC ACID; PROPYLENE GLYCOL; JOJOBA OIL

Active Ingredient

Tolnaftate 1%

Purpose

Antifungal

Warnings

Keep out of reach of children

Uses

Cures most Athlete’s Foot (Tinea Pedis) ■ Relieves itching, cracking, burning and scaling, which accompanies this condition ■
Prevents recurrence of Athlete’s Foot

Warnings

Do not use on children under 2 years of age ■ For external use only ■ Avoid contact with the eyes. If eye contact occurs, wash thoroughly with
water ■ Stop use and consult a physician if irritation occurs or if there is no improvement within four (4) weeks ■ Keep out of reach of children ■ If swallowed,
get medical help or contact a poison control center right away ■ If pregnant or breast-feeding, ask a health-care professional before use.

Directions

Wash the affected area with soap and water.
■ Dry thoroughly, then apply a thin layer over the affected area.
■ Use twice daily (morning and night) or as directed by a physician.
■ Pay special attention to the spaces between the toes and the areas around the edges and under the front of the nails.
■ Wear well-fitted ventilated shoes and change socks at least once daily.
■ Use daily for four (4) weeks. If condition persists longer, consult a physician.
■ Wash hands after each use. Store and use at room temperature.

Inactive Ingredeints

Inactive Ingredients: Ethyl Acetate, Isopropyl Alcohol, Isopropyl Myristate, Propylene Glycol, Water
Cosmetic Ingredients: Urea, Lactic Acid, Jojoba Oil, Undecylenic Acid, Dimethyl Isosorbide, Vitamin E